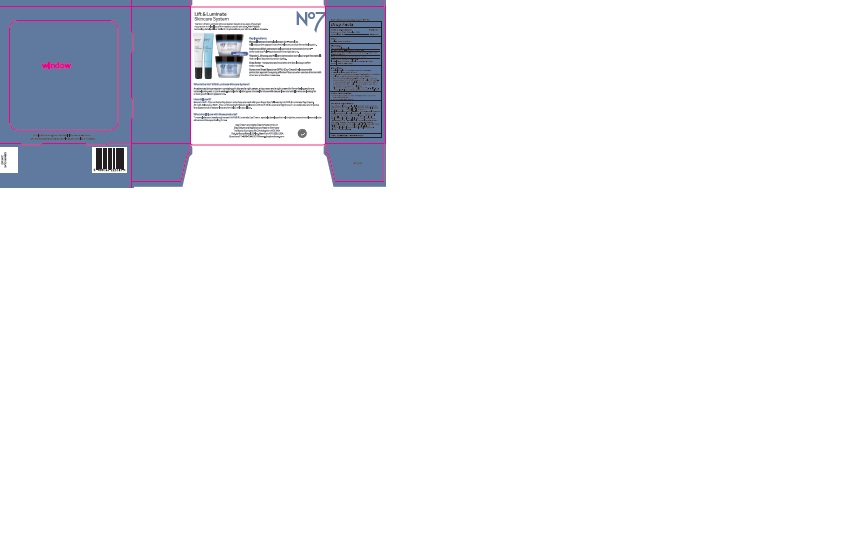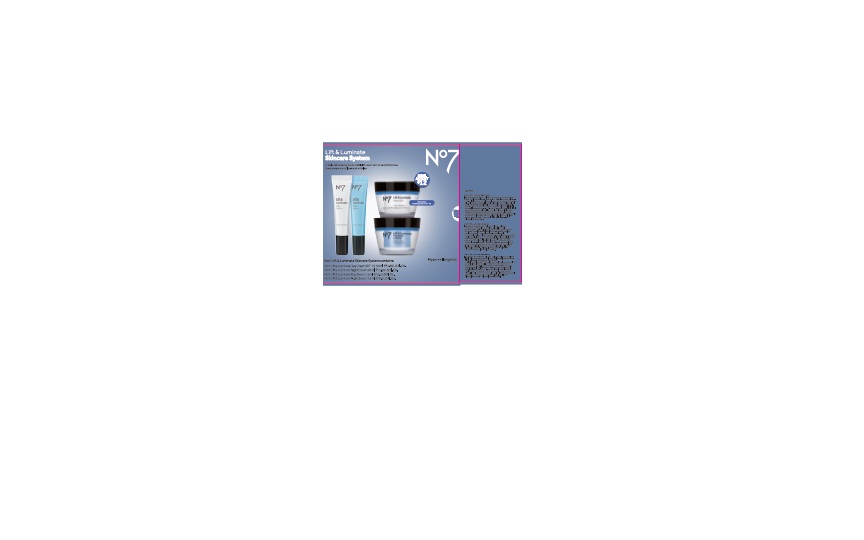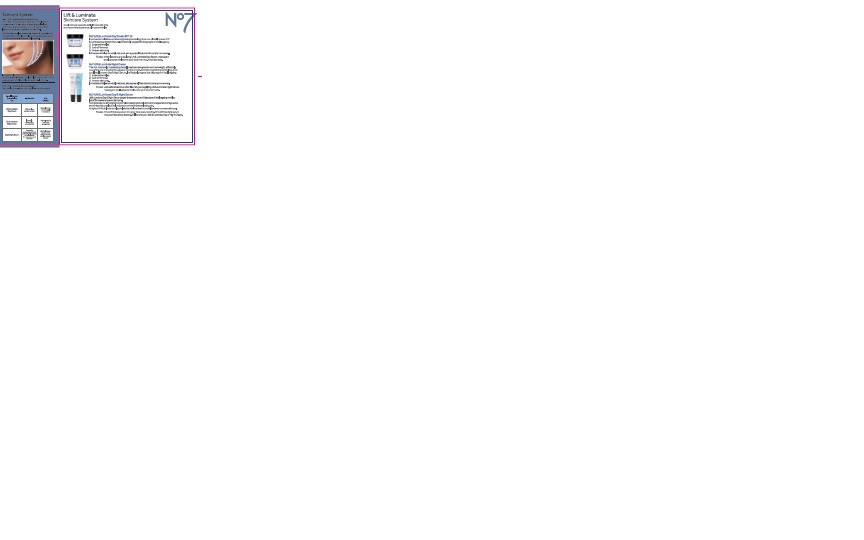 DRUG LABEL: No7 Lift and Luminate Day Cream SPF 15
NDC: 11489-099 | Form: CREAM
Manufacturer: BCM Ltd
Category: otc | Type: HUMAN OTC DRUG LABEL
Date: 20160203

ACTIVE INGREDIENTS: AVOBENZONE 1.5 g/50 g; OCTOCRYLENE 2 g/50 g; OCTISALATE 1 g/50 g
INACTIVE INGREDIENTS: WATER; GLYCERIN; C12-15 ALKYL BENZOATE; DIMETHICONE; MICA; CETEARYL GLUCOSIDE; TRIBEHENIN; AMMONIUM ACRYLOYLDIMETHYLTAURATE/VP COPOLYMER; PHENOXYETHANOL; DIPALMITOYL HYDROXYPROLINE; ALCOHOL; SHEA BUTTER; POTASSIUM CETYL PHOSPHATE; CITRIC ACID ACETATE; BUTYLENE GLYCOL; METHYLPARABEN; ETHYLPARABEN; XANTHAN GUM; DIPROPYLENE GLYCOL; VITAMIN A PALMITATE; ASCORBYL GLUCOSIDE; EDETATE SODIUM; TERT-BUTYL ALCOHOL; PANAX GINSENG ROOT OIL; LUPINUS ALBUS SEED; POLYSORBATE 20; POTASSIUM HYDROXIDE; ETHYLHEXYLGLYCERIN; TOCOPHEROL; ASCORBIC ACID; TITANIUM DIOXIDE; PALMITOYL TETRAPEPTIDE-7

No7 Lift and Luminate Day Cream Sunscreen Broad Spectrum SPF15

Carton Active Ingredients Section

Active ingredients

Avobenzone 3%

Octisalate 2%

Octocrylene 4%

Uses

Uses - helps prevent sunburn

Warnings

For external use only

Do not use on damaged or broken skin

When using this product keep out of eyes. Rinse with water to remove.

Ask a doctor

Stop use and ask a doctor if rash occurs

Keep out of reach of children

If swallowed, get medical help or contact a Poison Control Center right away

Directions

Apply liberally 15 minutes before sun exposure

reapply at least every 2 hours

use a water resistant sunscreen if swimming or sweating

children under 6 months of age: Ask a doctor

Sun Protection Measures. Spending time in the sun increases your risk of skin cancer and early skin aging.

To decrease this risk, regularly use a sunscreen with a Broad Spectrum SPF value of 15 or higher and other sun protection measures including:

Limit time in the sun, especially from 10 a.m - 2 p.m.

wear long-sleeved shirts,pants,hats and sunglasses.

Storage

Other information

Protect the product in this container from excessive heat and direct sun

Avoid contact with fabrics

Inactive ingredients

Aqua(Water), Glycerin, C12-15 alkyl benzoate, Dimethicone, Mica, Cetearyl glucoside, Tribehenin, Ammonium acryloydimethyltaurate/VP copolymer, Phenoxyethanol, Dipalmitoyl hydroxyproline, Alcohol, Butyrospermum parkii (Shea) butter, Potassium cetyl phosphate, Actinidia chinensis(Kiwi) fruit water, Cetearyl alcohol, Butylene glycol, Dimethiconol, Methylparaben, Parfum(Fragrance), Propylene glycol, Xanthan gum, Ethylparaben, Dipropylene glycol, Retinyl palmitate, Ascorbyl glucoside,, Tetrasodium EDTA, T-butyl alcohol, Lupinus albus seed extract, Carbomer, Citric acid, Panax ginseng root extract, Sophora angustifolia root extract,Polysorbate 20, Morus alba leaf extract, Ascorbic acid, Potassium hydroxide, Ethylhexylglycerin, Silica, Tocopherol, Palmitoyl tripeptide-1, Palmitoyl tetrapeptide-7, CI 77891(Titanium dioxide)

PATIENT COUNSELING INFORMATION

Made in the UK

The Boots Company PLC Nottingham England NG2 3AA

Dist. by Boots Retail USA Inc. Norwalk CT 06851 USA

www.boots.com

Description

Skincare System

No7 Lift and Luminate Day and Night Serum

No7 Lift and Luminate Day and Night Serum tackles the appearance of 3 main signs of ageing: wrinkles, loss of firmness and uneven skin tone in 4 weeks with skin looking younger and brighter from day one.

Skin firming complex containing Vitamin A, Peptides and an antioxidant complex to help improve skin texture and provide smoother and firmer feeling skin.

Independently proven to reduce the appearance of dark spots with a unique ant-ageing complex, it also works to reduce the appearance of wrinkles and leave the skin feeling firmer.

No7 Lift and Luminate Skincare System

Look visibly younger with this complete skincare regime

Reveal lifted and firmer-feeling skin | Key benefits | After 4 weeks
Lift and Luminate Day Cream | SPF15 helps prevent sunburn | Skin feels firmer and noticeably more radiant
Lift and Luminate Night Cream | Intensely moisturising and hydrating | Skin feels firmer and more even-toned
Day and Night Serum | Targets the appearance of 3 key signsof visible ageing: wrinkles, lack of firmness and uneven skin tone | Skin feels firmer, appears more even toned and wrinkles appear reduced

Lift and Luminate Skincare System

A daily skincare regime to visibly lift, even skin tone and improve the appearance of lines and wrinkles

No7 Lift and Luminate Day Cream SPF 15

Improved formulation contains brightening technology from our clinically proven Lift and Luminate Day and Night Serum. It effectively targets the 3 key signs of visble ageing:

1) Lines and wrinkles

2) Lack of firmness

3) Uneven skin tone.

In 2 weeks wrinkles are visibly reduced, skin appears lifted and skin tone is more even.

To use: After cleansing and applying Lift and Luminate Day Serum, massage in small upwards circles over your face and neck. Avoid eye area.

No7 Lift and Luminate Night Cream

This rich, intensively moisturising formula has been designed to work over-night, effectively nourishing and improving the appearance of your skin. Contains brightening technology from our clinically proven Day and Night Serum. It effectively targets the 3 key signs of visible ageing:

1) Lines and wrinkles

2) Lack of firmness

3) Uneven skin tone

In 4 weeks wrinkles are visibly reduced, skin appears lifted and skin tone is more even.

To use: Just before bedtime, after cleansing and applying Lift and Luminate Night Serum, massage in small upwards circles over your face and neck.

No7 Lift and Luminate Day and Night Serum

Lift and Luminate Day and Night Serum targets the appearance of 3 key sighns of visble ageing: wrinkles, lack of firmness and uneven skin tone.

During the day, our skin brightening complex is designed to help diminish the appearance of age spots, and our firming complex to help provide smoother and firmer looking skin. At night, a PHA is included to help exfoliate the skin's surface for a revitalised and more even skin tone.

To use: Smooth the day serum into your face every morning. Smooth the night serum into your face every evening. Follow with your Lift and Luminate Day or Night Cream

Description

Lift and Luminate Skincare System

The No7 Lift and Luminate Skincare System targets 3 key signs of ageing in mature skin: wrinkles, loss of firmness and uneven skin tone. With Peptide technology to help deliver visible firming benefits to your skin in as little as 4 weeks.

Key Ingredients

Matrixyl 300 and retinyl palmitate (pro-retinol) to help reduce the appearance of wrinkles and provide firmer feeling skin.

Sophora and kiwi extracts to help provide a more even skin tone enhanced by a Poly-hydroxyacid in the night serum.

Vitamin C, Ginseng and Mulberry (antioxidant complex) target free radicals that can lead to premature ageing

Shea Butter moisturises and nourishes the skin, leaving it softer and smoother.

Sunscreen Broad Spectrum SPF15 (Day Cream) helps to provide protection against the ageing effects of the sun when used as directed with other sun protection measures.

What is the No7 Lift and Luminate Skincare System

An advanced skincare system consistin of a day and a night serum, a day cream and a night cream for firmer feeling and more radiant looking skin in just 4 weeks. Suitable for all skin types, it is ideal for those with deeper lines and wrinkles who are looking for a more youthful skin appearance.

How do I use it

Smooth No7 Lift and Luminate Day Serum onto face and neck with your finger tips, followed by No7 Lift and Luminate Day Cream. At nigh follow your No7 Lift and Luminate Night Serum application with No7 Lift and Luminate Night Cream to moisturise and improve the appearance of deeper lines and wrinkles while you sleep.

What should I use with these products

To complete your beauty regime use No7 Lift and Luminate Eye Cream specially developed to help brighten, smooth and leave delicate skin around the eyes feeling firmer

Day Cream and Night Cream Made in the UK

Day Serum and Night Serum Made in Germany

The Boots Company PLC Nottingham NG2 3AA

Dist. by Boots Retail USA Inc. New York NY 1005 USA

Questions 1-866-75-BOOTS/www.shopbootsusa.com